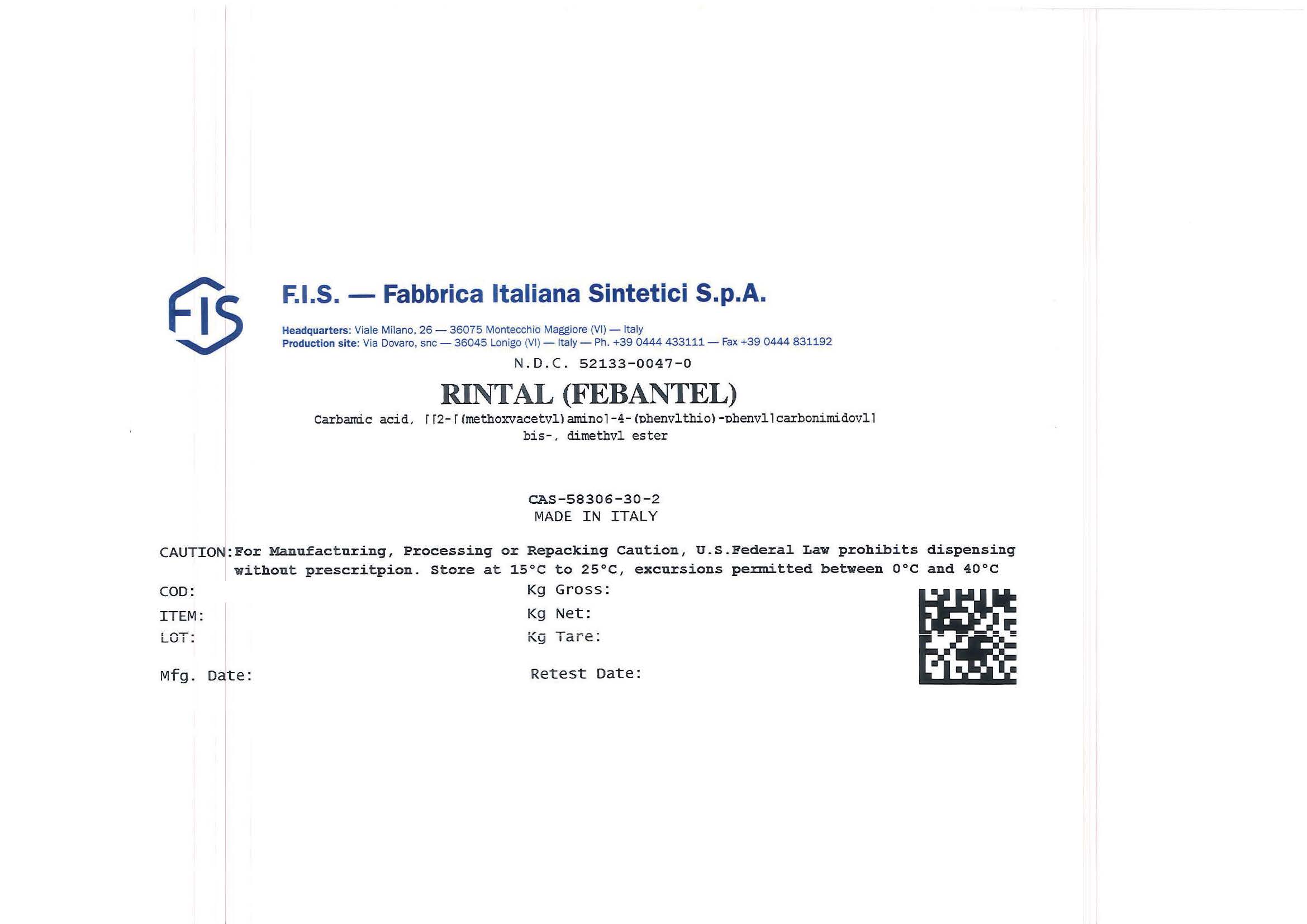 DRUG LABEL: FEBANTEL
NDC: 52133-0047 | Form: POWDER
Manufacturer: F.I.S. Fabbrica Italiana Sintetici  S.P.A.
Category: other | Type: BULK INGREDIENT - ANIMAL DRUG
Date: 20241122

ACTIVE INGREDIENTS: FEBANTEL 1 kg/1 kg

Febantel